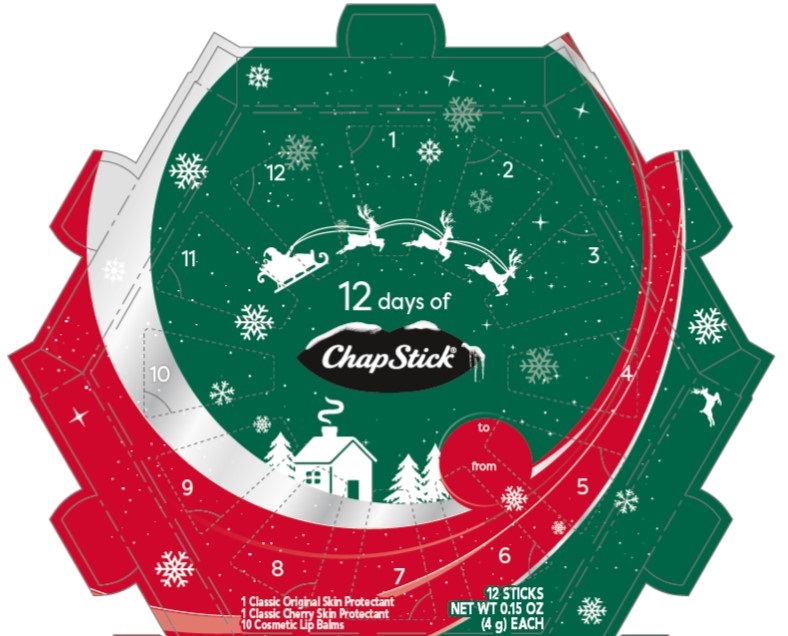 DRUG LABEL: Chapstick
NDC: 0135-2029 | Form: KIT | Route: TOPICAL
Manufacturer: Haleon US Holdings LLC
Category: otc | Type: HUMAN OTC DRUG LABEL
Date: 20240411

ACTIVE INGREDIENTS: PETROLATUM 450 mg/1 g; PETROLATUM 450 mg/1 g
INACTIVE INGREDIENTS: CAMPHOR (NATURAL); CARNAUBA WAX; CETYL ALCOHOL; ISOPROPYL MYRISTATE; LANOLIN; LIGHT MINERAL OIL; OCTYLDODECANOL; OLEYL ALCOHOL; PARAFFIN; PHENYL TRIMETHICONE; D&C RED NO. 6; TITANIUM DIOXIDE; WHITE WAX; FD&C YELLOW NO. 5; ARACHIDYL PROPIONATE; CAMPHOR (NATURAL); CARNAUBA WAX; CETYL ALCOHOL; ISOPROPYL MYRISTATE; LANOLIN; LIGHT MINERAL OIL; LEVOMENTHOL; OCTYLDODECANOL; PARAFFIN; PHENYL TRIMETHICONE; D&C RED NO. 6; SACCHARIN; WHITE WAX

Drug Facts

Classic Original | Cherry

Active ingredient

White Petrolatum 45%

Purpose

Skin Protectant

Uses

- helps prevent and temporarily protects chafed, chapped or cracked lips
- helps prevent and protect from the drying effects of wind and cold weather

Warnings

For external use only

Keep Out of Reach of Children

If swallowed, get medical help or contact a Poison Control Center right away.

Directions

apply as needed

Other Information

store at 20-25°C (68-77°F)

Inactive ingredients (Classic Original)

arachidyl propionate, camphor, carnauba wax, cetyl alcohol, fragrance, isopropyl lanolate, isopropyl myristate, lanolin, light mineral oil, octyldodecanol, oleyl alcohol, paraffin, phenyl trimethicone, red 6 lake, titanium dioxide, white wax, yellow 5 lake

Inactive ingredients (Classic Cherry)

arachidyl propionate, camphor, carnauba wax, cetyl alcohol, fragrance, isopropyl lanolate, isopropyl myristate, lanolin, light mineral oil, menthol, octyldodecanol, paraffin, phenyl trimethicone, red 6 lake, saccharin, white wax

Questions or Comments?

Call weekdays from 9 AM to 5 PM EST at 1-877-227-3421

Cosmetic Lip Balms

Ingredients (Clover Honey)

petrolatum, paraffin, mineral oil, octyldodecanol, canola oil, bis-diglyceryl polyacyladipate-2, arachidyl propionate, phenyl trimethicone, beeswax, copernicia cerifera (carnauba) wax, isopropyl myristate, cetyl alcohol, lecithin (soy), flavor, saccharin, synthetic wax, iron oxides, isopropyl titanium triisostearate

Ingredients (Cake Batter)

petrolatum, paraffin, mineral oil, octyldodecanol, bis-diglyceryl polyacyladipate-2, caprylic/capric triglyceride, phenyl trimethicone, arachidyl propionate, beeswax, isopropyl myristate, copernicia cerifera (carnauba) wax, lecithin (soy), cetyl alcohol, flavor, triacetin, benzyl benzoate, saccharin, titanium dioxide, synthetic wax, isopropyl titanium triisostearate

Ingredients (Cotton Candy)

petrolatum, paraffin, mineral oil, octyldodecanol, bis-diglyceryl polyacyladipate-2, arachidyl propionate, phenyl trimethicone, beeswax, benzyl benzoate, copernicia cerifera (carnauba) wax, isopropyl myristate, cetyl alcohol, lecithin (soy), flavor, saccharin, synthetic wax, blue 1 lake, isopropyl titanium triisostearate

Ingredients (Passion Fruit)

petrolatum, paraffin, mineral oil, octyldodecanol, bis-diglyceryl polyacyladipate-2, canola oil, arachidyl propionate, phenyl trimethicone, beeswax, copernicia cerifera (carnauba) wax, isopropyl myristate, flavor, cetyl alcohol, lecithin (soy), saccharin, synthetic wax, iron oxides, yellow 6 lake, isopropyl titanium triisostearate

Ingredients (Holiday Cocoa)

petrolatum, paraffin, mineral oil, octyldodecanol, bis-diglyceryl polyacyladipate-2, caprylic/capric triglyceride, arachidyl propionate, phenyl trimethicone, beeswax, copernicia cerifera (carnauba) wax, isopropyl myristate, cetyl alcohol, lecithin (soy), flavor, saccharin, synthetic wax, yellow 5 lake, blue 1 lake, isopropyl titanium triisostearate

Ingredients (Vanilla Latte)

petrolatum, paraffin, mineral oil, octyldodecanol, bis-diglyceryl polyacyladipate-2, caprylic/capric triglyceride, phenyl trimethicone, arachidyl propionate, beeswax, copernicia cerifera (carnauba) wax, isopropyl myristate, cetyl alcohol, flavor, titanium dioxide, synthetic wax, saccharin, triacetin, iron

oxides, isopropyl titanium triisostearate

Ingredients (Pumpkin Pie)

petrolatum, paraffin, mineral oil, octyldodecanol, bis-diglyceryl polyacyladipate-2, arachidyl propionate, phenyl trimethicone, beeswax, caprylic/capric triglyceride, copernicia cerifera (carnauba) wax, isopropyl myristate, flavor, cetyl alcohol, lecithin (soy), triacetin, synthetic wax, saccharin, iron oxides, titanium dioxide, yellow 6 lake, isopropyl titanium triisostearate

Ingredients (Sugar Cookie)

petrolatum, paraffin, mineral oil, octyldodecanol, bis-diglyceryl polyacyladipate-2, arachidyl propionate, phenyl trimethicone, beeswax, caprylic/capric triglyceride, flavor, copernicia cerifera (carnauba) wax, isopropyl myristate, cetyl alcohol, benzyl benzoate, triacetin, saccharin

Ingredients (Candy Cane)

petrolatum, paraffin, mineral oil, octyldodecanol, bis-diglyceryl polyacyladipate-2, flavor, arachidyl propionate, phenyl trimethicone, beeswax, copernicia cerifera (carnauba) wax, isopropyl myristate, cetyl alcohol, titanium dioxide, synthetic wax, saccharin, canola oil, isopropyl titanium triisostearate

Ingredients (Vanilla Mint)

petrolatum, paraffin, mineral oil, octyldodecanol, bis-diglyceryl polyacyladipate-2, caprylic/capric triglyceride, arachidyl propionate, phenyl trimethicone, beeswax, copernicia cerifera (carnauba) wax, isopropyl myristate, flavor, cetyl alcohol, lecithin (soy), ethyl alcohol, saccharin

Other Information

store at 20-25°C (68-77°F)

Additional Information

Distributed by: GSK Consumer Healthcare, Warren, NJ 07059

For most recent product information, visit www.chapstick.com

Trademarks owned or licensed by GSK

©2021 GSK or licensor

PRINCIPAL DISPLAY PANEL

NDC 0573-2028-01

12 days of

ChapStick®

to

from

- 1 Classic Original Skin Protectant
- 1 Classic Cherry Skin Protectant
- 10 Cosmetic Lip Balms

12 STICKS

NET WT 0.15 OZ

(4 g) EACH

000065947 – Front